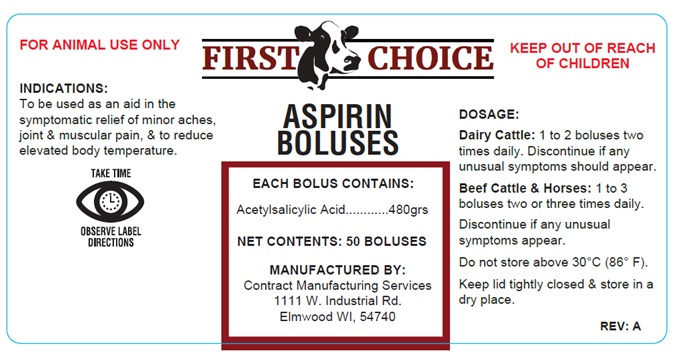 DRUG LABEL: FIRST CHOICE ASPIRIN BOLUS - 480grs
NDC: 86158-2086 | Form: TABLET
Manufacturer: Contract Manufacturing Services, LLC
Category: animal | Type: OTC ANIMAL DRUG LABEL
Date: 20250217

ACTIVE INGREDIENTS: ASPIRIN 32 g/1 1
INACTIVE INGREDIENTS: STARCH, CORN

FIRST CHOICE ASPIRIN BOLUSES

EACH BOLUS CONTAINS:

Acetylsalicylic Acid............480grs

DOSAGE:

Dairy Cattle: 1 to 2 boluses two times daily. Discontinue if any unusual symptoms should appear.

Beef Cattle & Horses: 1 to 3 boluses two or three times daily.

Discontinue if any unusual symptoms appear.

STORAGE AND HANDLING

Do not store above 30°C (86° F).

Keep lid tightly closed & store in a dry place.

INDICATIONS:

To be used as an aid in the symptomatic relief of minor aches, joint & muscular pain, & to reduce elevated body temperature.

WARNINGS

FOR ANIMAL USE ONLY

KEEP OUT OF REACH OF CHILDREN

MANUFACTURED BY:
Contract Manufacturing Services
1111 W. Industrial Rd.
Elmwood WI, 54740

TAKE TIME

OBSERVE LABEL DIRECTIONS